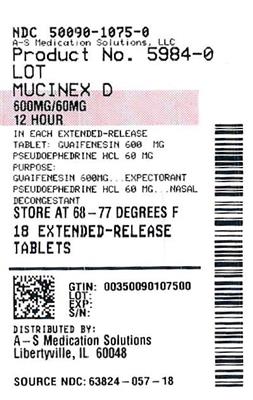 DRUG LABEL: Mucinex D
NDC: 50090-1075 | Form: TABLET, EXTENDED RELEASE
Manufacturer: A-S Medication Solutions
Category: otc | Type: HUMAN OTC DRUG LABEL
Date: 20250623

ACTIVE INGREDIENTS: GUAIFENESIN 600 mg/1 1; PSEUDOEPHEDRINE HYDROCHLORIDE 60 mg/1 1
INACTIVE INGREDIENTS: CARBOMER HOMOPOLYMER TYPE B (ALLYL PENTAERYTHRITOL CROSSLINKED); CI 15985; ALUMINA; HYDROXYPROPYL METHYLCELLULOSE; MAGNESIUM STEARATE; MICROCRYSTALLINE CELLULOSE

Mucinex®D

Drug Facts

ACTIVE INGREDIENT

PURPOSE

Active ingredients (in each extended-release tablet) | Purposes
Guaifenesin 600 mg | Expectorant
Pseudoephedrine HCl 60 mg | Nasal Decongestant

Uses

- helps loosen phlegm (mucus) and thin bronchial secretions to rid the bronchial passageways of bothersome mucus and make coughs more productive
- temporarily relieves nasal congestion due to:
  - common cold
  - hay fever
  - upper respiratory allergies
- temporarily restores freer breathing through the nose
- promotes nasal and/or sinus drainage
- temporarily relieves sinus congestion and pressure

Warnings

DO NOT USE

Do not useif you are now taking a prescription monoamine oxidase inhibitor (MAOI) (certain drugs for depression, psychiatric, or emotional conditions, or Parkinson's disease), or for 2 weeks after stopping the MAOI drug. If you do not know if your prescription drug contains an MAOI, ask a doctor or pharmacist before taking this product.

Ask a doctor before use if you have

- heart disease
- high blood pressure
- thyroid disease
- diabetes
- trouble urinating due to an enlarged prostate gland
- persistent or chronic cough such as occurs with smoking, asthma, chronic bronchitis, or emphysema
- cough accompanied by too much phlegm (mucus)

When using this product

- do not use more than directed

Stop use and ask a doctor if

- you get nervous, dizzy, or sleepless
- symptoms do not get better within 7 days, come back or occur with a fever, rash, or persistent headache. These could be signs of a serious illness.

PREGNANCY OR BREAST FEEDING

If pregnant or breast-feeding,ask a health professional before use.

Keep out of reach of children.In case of overdose, get medical help or contact a Poison Control Center right away.

Directions

- do not crush, chew, or break extended-release tablet
- take with a full glass of water
- this product can be administered without regard for timing of meals
- adults and children 12 years and older: 2 extended-release tablets every 12 hours; not more than 4 extended-release tablets in 24 hours
- children under 12 years of age: do not use

Other information

- tamper evident: do not use if carton is open or if printed seal on blister is broken or missing
- store at 20-25°C (68-77°F)

Inactive ingredients

carbomer homopolymer type B; FD&C yellow no. 6 aluminum lake; hypromellose, USP; magnesium stearate, NF; microcrystalline cellulose, NF; sodium starch glycolate, NF

Questions?

1-866-MUCINEX (1-866-682-4639)

Dist. by: RB Health (US)
Parsippany, NJ 07054-0224
Made in England